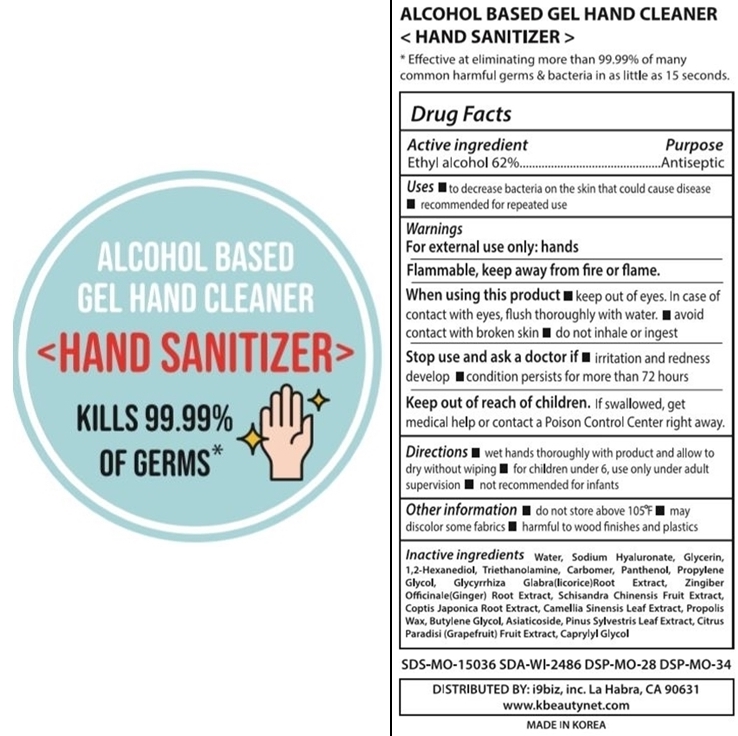 DRUG LABEL: HAND CLEANER HAND SANITIZER
NDC: 74429-311 | Form: GEL
Manufacturer: i9biz, Inc
Category: otc | Type: HUMAN OTC DRUG LABEL
Date: 20200402

ACTIVE INGREDIENTS: ALCOHOL 62.035 mL/100 mL
INACTIVE INGREDIENTS: WATER 35.2245 mL/100 mL; GLYCERIN 0.45 mL/100 mL; HYALURONATE SODIUM 0.005 mL/100 mL; 1,2-HEXANEDIOL 0.03 mL/100 mL; PROPYLENE GLYCOL 0.2 mL/100 mL; COPTIS JAPONICA ROOT 0.005 mL/100 mL; PROPOLIS WAX 0.0025 mL/100 mL; BUTYLENE GLYCOL 0.055 mL/100 mL; CAPRYLYL GLYCOL 0.0025 mL/100 mL; TROLAMINE 0.35 mL/100 mL; CARBOMER HOMOPOLYMER, UNSPECIFIED TYPE 0.35 mL/100 mL; PANTHENOL 0.3 mL/100 mL; GLYCYRRHIZA GLABRA 0.05 mL/100 mL; SCHISANDRA CHINENSIS FRUIT 0.005 mL/100 mL; GINGER 0.005 mL/100 mL; GREEN TEA LEAF 0.005 mL/100 mL; ASIATICOSIDE 0.0005 mL/100 mL; GRAPEFRUIT 0.435 mL/100 mL; PINE NEEDLE OIL (PINUS SYLVESTRIS) 0.49 mL/100 mL

Active Ingredient

Ethyl alcohol 62%

Purpose

Antiseptic

Uses

to decrease bacteria on the skin that could cause disease

recommended for repeated use

Warnings

For external use only: hands

Flammable, keep away from fire or flame

When using this product

keep out of eyes. In case of contact with eyes, flush thoroughly with water.

avoid contact with broken skin

do not inhale or ingest

Stop use and ask a doctor if

irritation and redness develop

condition persists for more than 72 hours

Directions

wet hands thoroughly with product and allow to dry without wiping

for children under 6, use only under adult supervision

not recommended for infants

Other information

do not store above 105F

may discolor some fabrics

harmful to wood finishes and plastics

Inactive ingredients

Water, Sodium Hyaluronate, Glycerin, 1,2-Hexanediol, Triethanolamine, Carbomer, Panthenol, Propylene Glycol, Glycyrrhiza Glabra (licorice) Root Extract, Zingiber Officinale (Ginger) Root Extract, Schisandra Chinensis Fruit Extract, Coptis Japonica Root Extract, Camellia Sinensis Leaf Extract, Propolis Wax, Butylene Glycol, Asiaticoside, Citrus Paradisi (Grapefruit) Fruit Extract, Pinus Sylvestris Leaf Extract, Caprylyl Glycol

Keep out of reach of children

If swallowed, get medical help or contact a Poison Control Center right away.